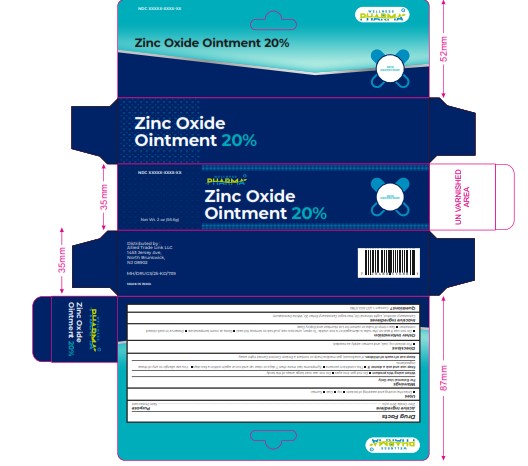 DRUG LABEL: ZINC OXIDE PHARMA
NDC: 84387-001 | Form: OINTMENT
Manufacturer: ALLIED TRADE LINK LLC
Category: otc | Type: HUMAN OTC DRUG LABEL
Date: 20241029

ACTIVE INGREDIENTS: ZINC OXIDE 200 mg/1 g
INACTIVE INGREDIENTS: WHITE PETROLATUM; CETOSTEARYL ALCOHOL; LIGHT MINERAL OIL; POLYOXYL 20 CETOSTEARYL ETHER

HUMAN OTC DRUG LABEL

DOSAGE

Active Ingredient Purpose
Zinc Oxide 20% w/w .

WARNINGS

For External Use Only
When using this product Do not get into eyes Do not use over large areas of the body
Stop use and ask a doctor if The condition worsens Symptoms last more than 7 days or clear up and occur again within a few days You are allergic to any of these
ingredients
Keep out of reach of children. If swallowed, get medical help or contact a Poison Control Center right away.

INACTIVE

Inactive Ingredients
Cetostearyl Alcohol, Light Mineral Oil, Macrogol Cetostearyl Ether 20, White Petrolatum

Directions
For poison ivy, oak, and sumac: apply as needed.

Uses
Dries the oozing and weeping of poison: Ivy Oak Sumac

KEEP OUT OF REACH OF CHILDREN

PURPOSE SINK PROTECTANT

OXIDE ZINC

OXIDE OINMENT